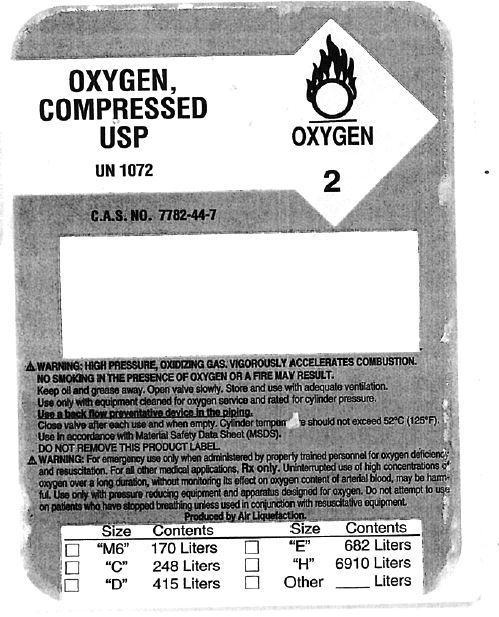 DRUG LABEL: Oxygen
NDC: 64960-000 | Form: GAS
Manufacturer: King's Daughters Home Medical Equipment
Category: prescription | Type: HUMAN PRESCRIPTION DRUG LABEL
Date: 20130730

ACTIVE INGREDIENTS: OXYGEN 1 L/1 L

Oxygen, Compressed USP